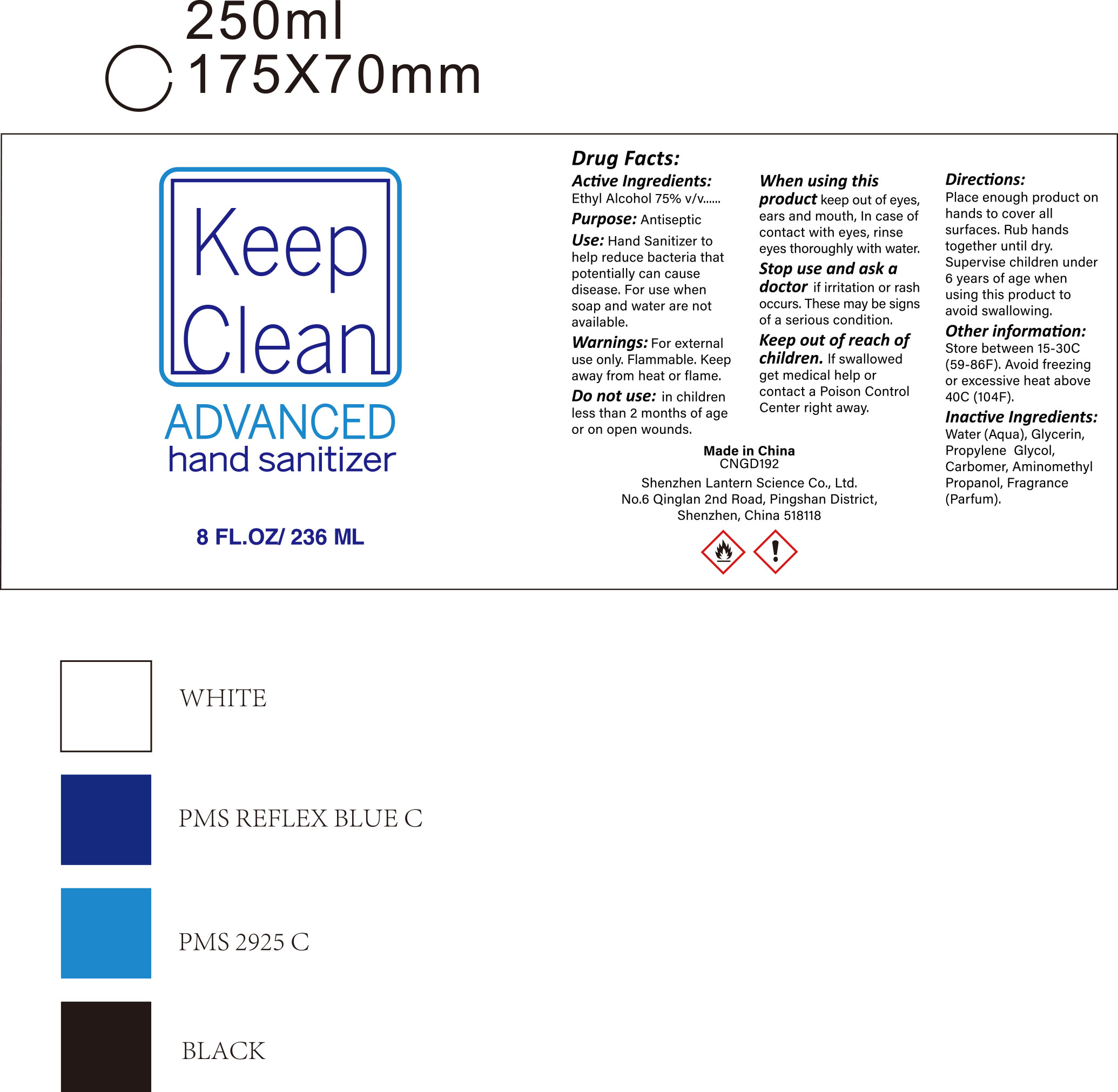 DRUG LABEL: hand sanitizer 8oz
NDC: 54860-270 | Form: LIQUID
Manufacturer: Shenzhen Lantern Scicence Co Ltd
Category: otc | Type: HUMAN OTC DRUG LABEL
Date: 20200920

ACTIVE INGREDIENTS: ALCOHOL 71 g/100 g
INACTIVE INGREDIENTS: PROPYLENE GLYCOL 0.01 g/100 g; LEMON 0.1 g/100 g; CARBOMER 940 0.35 g/100 g; AMINOMETHYLPROPANOL 0.11 g/100 g; WATER 28.42 g/100 g; GLYCERIN 0.01 g/100 g

Hand sanitizer 8oz

Active Ingredient

Active Ingredient purpose

Ethyl Alcohol 75%(v/v) Antiseptic

USE

Hand sanitizer to help reduce bacteria that potentiallycan cause disease.For use when soap and water are not available.

DOSAGE AND ADMINISTRATION

Recommended for repeated use.

use anywhere without water.

Warning

For external use only.Flammable.Keep away from heat or flame.

WARNINGS AND PRECAUTIONS

For external use only.

Flammable, keep away from heat and flame.

STOP USE

Discontinue if skin becomes irritated and ask a doctor .

Keep out of reach of children. In case of accidental ingestion, seek professional assistance or contact a poson control center immediately.

Inavtive ingredients

Water, Glycerin,Propylene Glycol,Carbomer,,Aminomethyl propanol,Fragrance(parfum).

Directions

place enough product on hands to cover all surfaces,Rub hands together until dry.

supervise children under 6 years of age when using this product to avoid swallowing.

When using this product

keep out of eyes. In case of contact with eyes, flush thoroughly with water.

Do not inhale or ingest.

Avoid contact with broken skin.

Other information

Do not store above 105F.

May discolor some fabrics.

Harmful to wood finishes and plastics.

Do not use

In children less than 2 months of age or on open wounds

when using this product

keep out of eyes,ears and mouth,in case of contact with eyes,rinse eyes thoroughly with water.

keep out of reach of children

If swallowed,get medical help or contact a poison control center right away.

other information

between 15-30℃（59-86℉）。Avoid freezing and excessive heat above 40℃（104℉）.